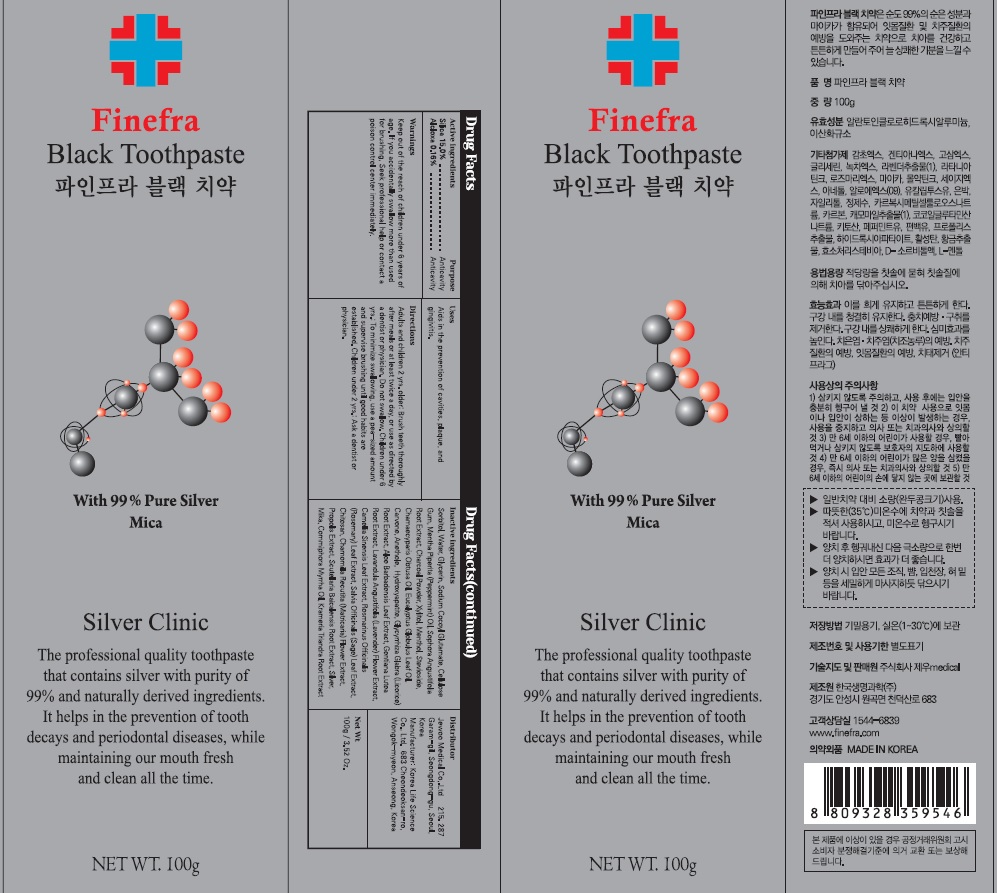 DRUG LABEL: Finefra Black Tooth
NDC: 69653-100 | Form: PASTE, DENTIFRICE
Manufacturer: Jewoo Medical Co,.Ltd
Category: otc | Type: HUMAN OTC DRUG LABEL
Date: 20200210

ACTIVE INGREDIENTS: SILICON DIOXIDE 15.0 g/100 g; ALCLOXA 0.16 g/100 g
INACTIVE INGREDIENTS: SORBITOL; Water

ACTIVE INGREDIENT

Active ingredients: Silica 15.00%, Alcloxa 0.16%

INACTIVE INGREDIENT

Inactive ingredients:

Sorbitol, Water, Glycerin, Sodium Cocoyl Glutamate, Cellulose Gum, Mentha Piperita (Peppermint) Oil, Sophora Angustifolia Root Extract, Charcoal Powder, Xylitol, Menthol, Stevioside, Chamaecyparis Obtusa Oil, Eucalyptus Globulus Leaf Oil, Carvone, Anethole, Hydroxyapatite, Glycyrrhiza Glabra (Licorice) Root Extract, Aloe Barbadensis Leaf Extract, Gentiana Lutea Root Extract, Lavandula Angustifolia (Lavender) Flower Extract, Camellia Sinensis Leaf Extract, Rosmarinus Officinalis (Rosemary) Leaf Extract, Salvia Officinalis (Sage) Leaf Extract, Chitosan, Chamomilla Recutita (Matricaria) Flower Extract, Propolis Extract, Scutellaria Baicalensis Root Extract, Silver, Mika, Commiphora Myrrha Oil, Krameria Triandra Root Extract

PURPOSE

Purpose: Anticavity

WARNINGS

Keep out of the reach of children under 6 years of age.
If you accidentally swallow more than used for brushing, Seek professional help or contact a poison control center immediately

KEEP OUT OF REACH OF CHILDREN

Keep out of the reach of children under 6 years of age.

Uses

Aids in the prevention of cavities, plaque, and gingivitis.

Directions

Adults and children 2 yrs. older: Brush teeth thoroughly after meals or at least twice a day, or use as directed by a dentist or physician. Do not swallow. Children under 6 yrs.: To minimize swallowing, use a pea-sized amount and supervise brushing until good habits are established. Children under 2 yrs.: Ask a dentist or physician.